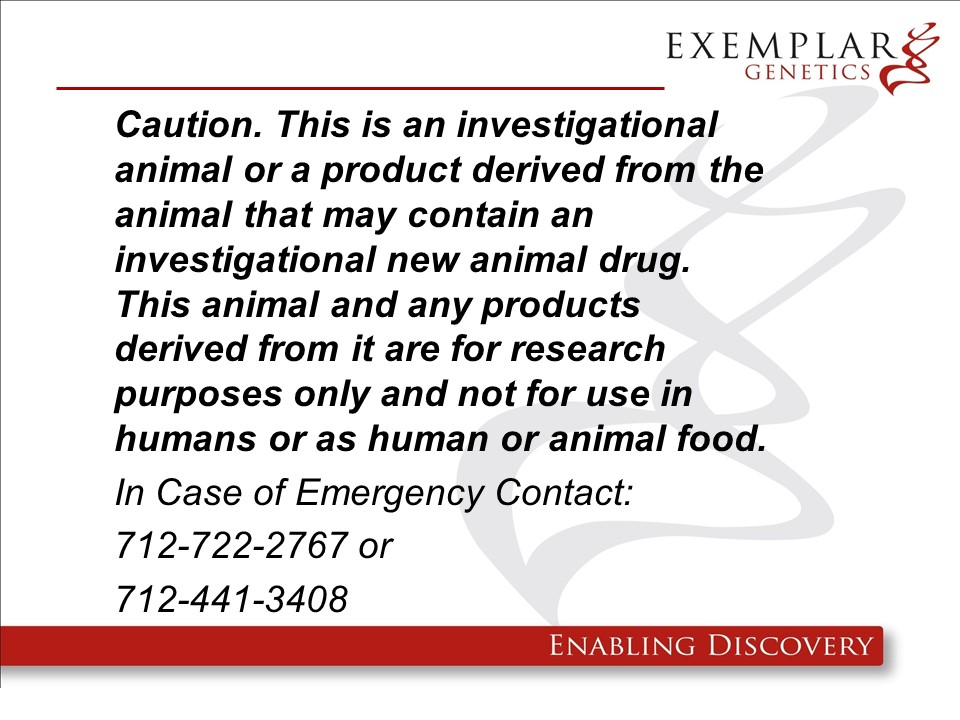 DRUG LABEL: ExeGen MYH7 miniswine
NDC: 86093-2003 | Form: NOT APPLICABLE
Manufacturer: Exemplar Genetics LLC (dba Precigen Exemplar)
Category: other | Type: INTENTIONAL ANIMAL GENOMIC ALTERATION LABEL
Date: 20250521

ACTIVE INGREDIENTS: MYH7 RDNA CONSTRUCT DISRUPTING EXON 13 OF MYH7 GENE IN YUCATAN MINIATURE SWINE 1 [arb'U]/1 [arb'U]

pMYH7 in miniswine

ExeGen MYH7 miniswine are genetically engineered yucatan miniature swine containing the rDNA construct pMYH7-Blast which exhibit similar phenotypes to human patients with HCM. These pigs are intended to be used as large animal models of the human disease. We will not be requesting a food use authorization and the carcasses and all materials generated from these animals will be destroyed by incineration.

Product Definition: A specific line of Yucatan miniature pigs (Sus scrofa domesticus), including heterozygous offspring resulting from a heterozygous founder, in which the MYH7 gene has been disrupted by the homologous recombination of a single copy of a mutated MYH7-PGK construct resulting in the mutation R403Q for use in biomedical research. The final sellable animal well be a heterozygote MYH7 +/R403Q Blast Excised miniswine.

Warning: This product is from a genetically engineered animal and may contain an investigational new animal drug. It is for research purposes only and not for use in humans or as food/feed unless authorization has been granted by the US Food and Drug Administration. In case of emergency release contact Exemplar Genetics at 712-722-2767 or 712-441-3408.